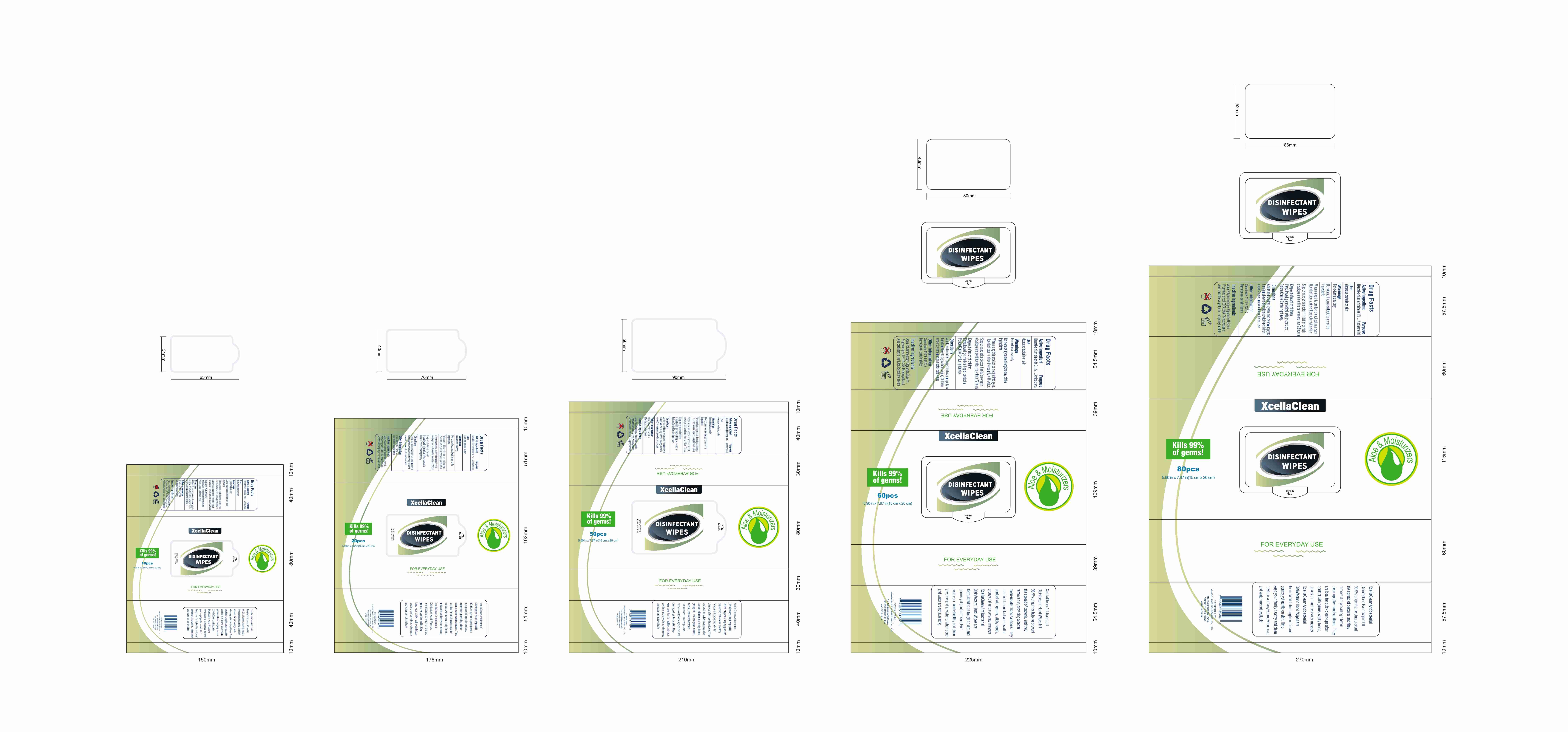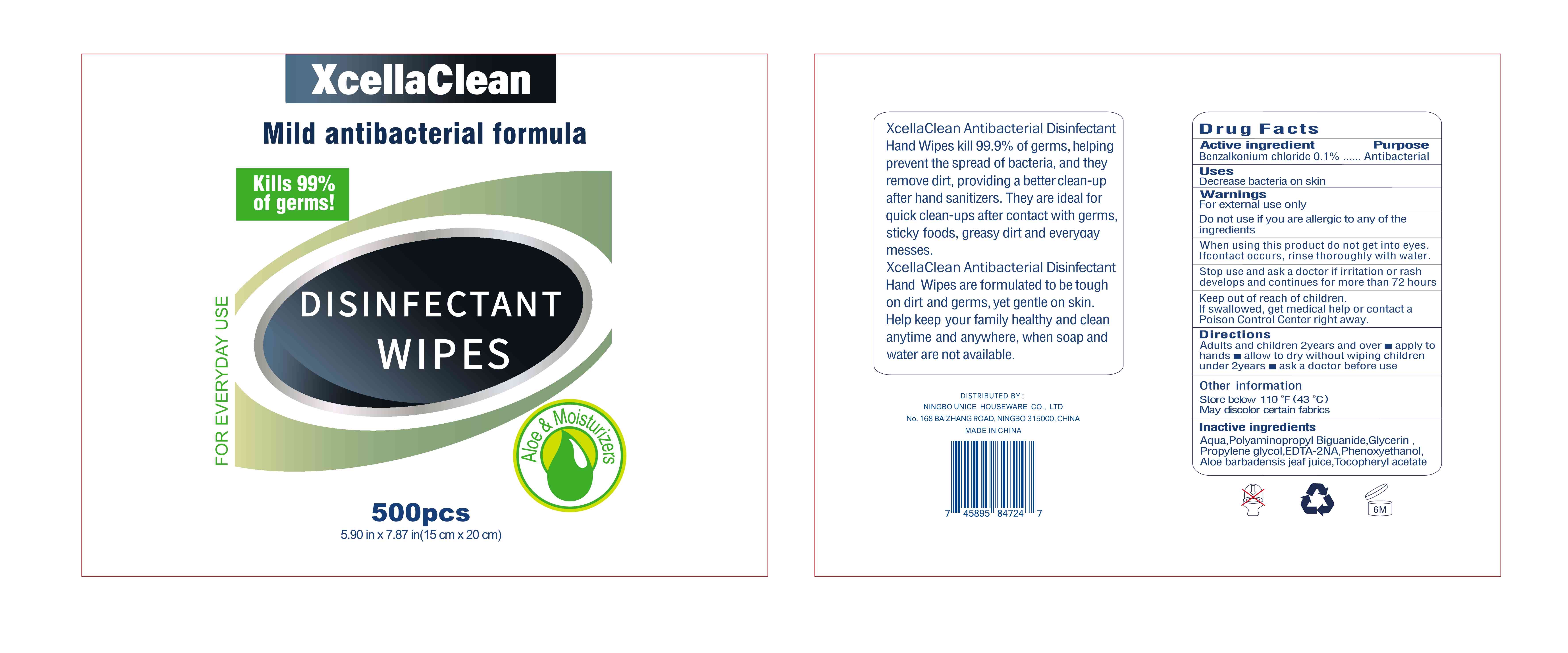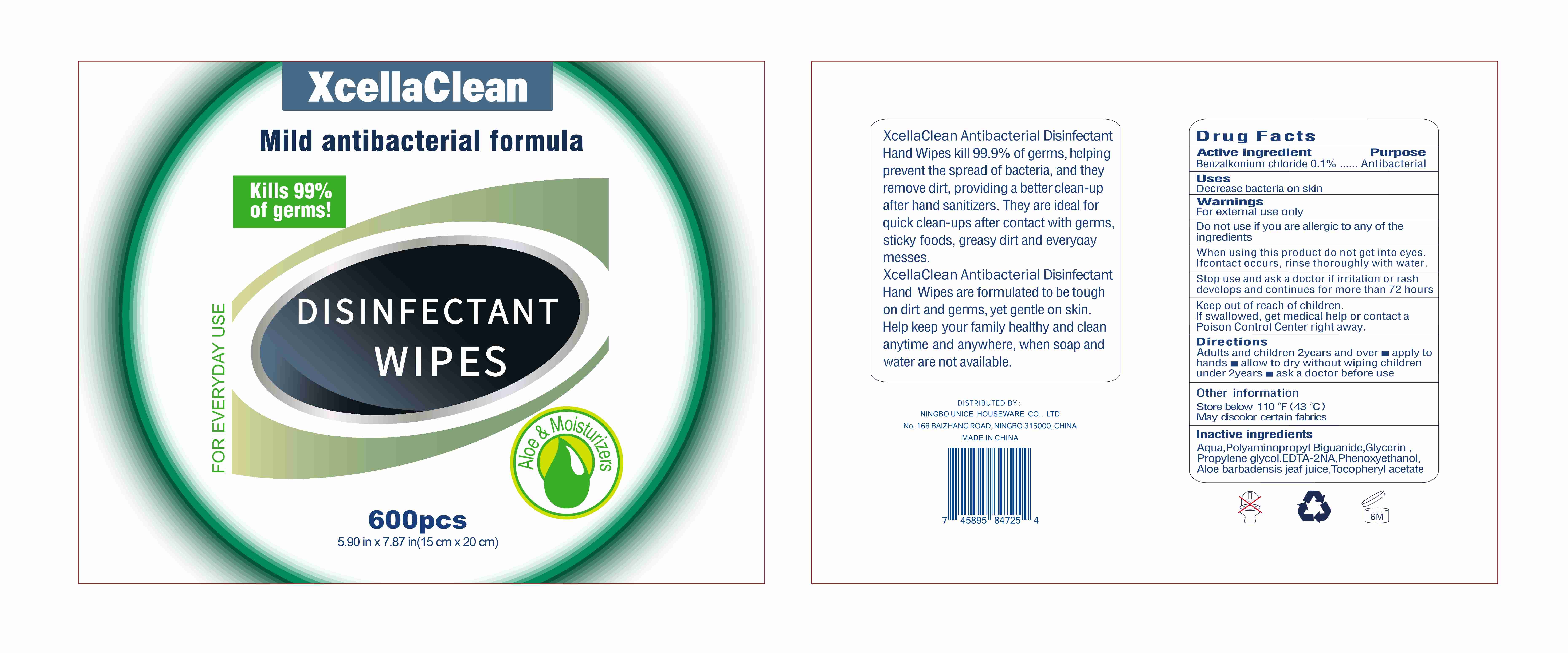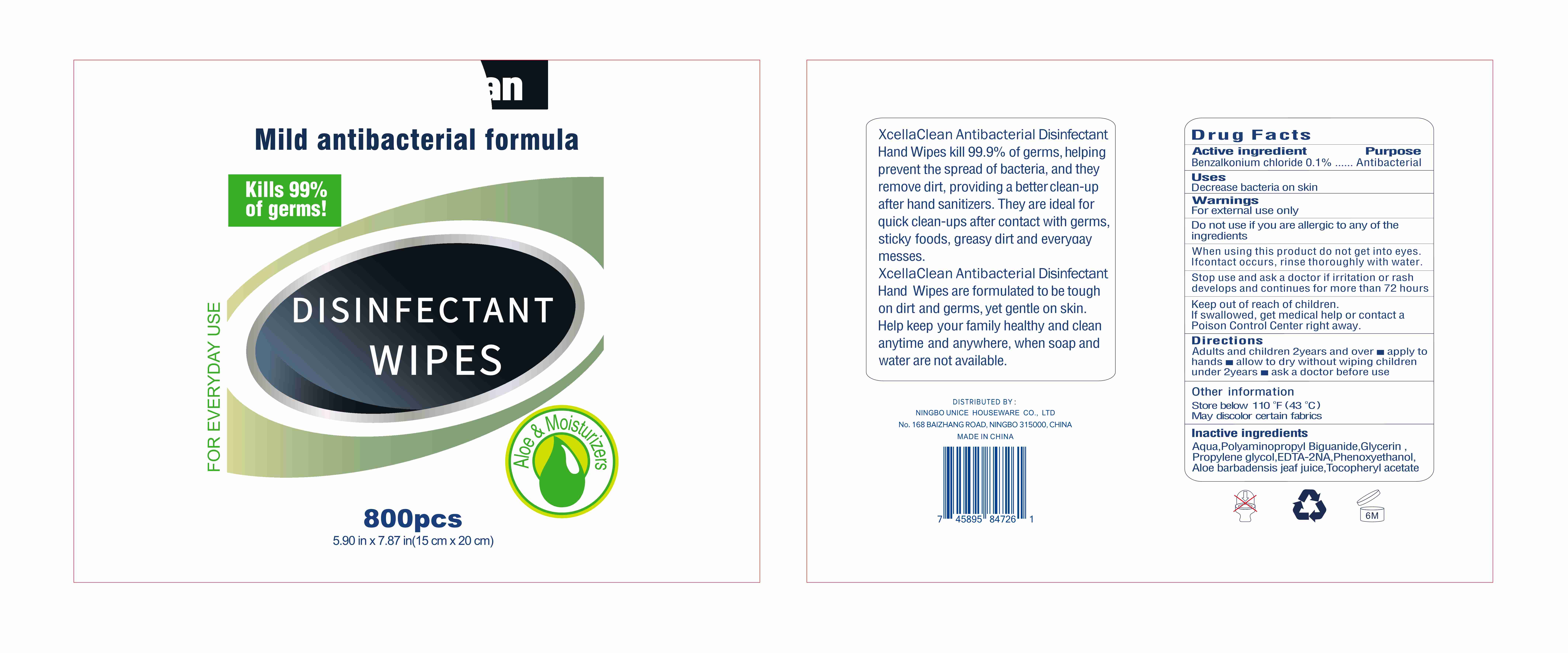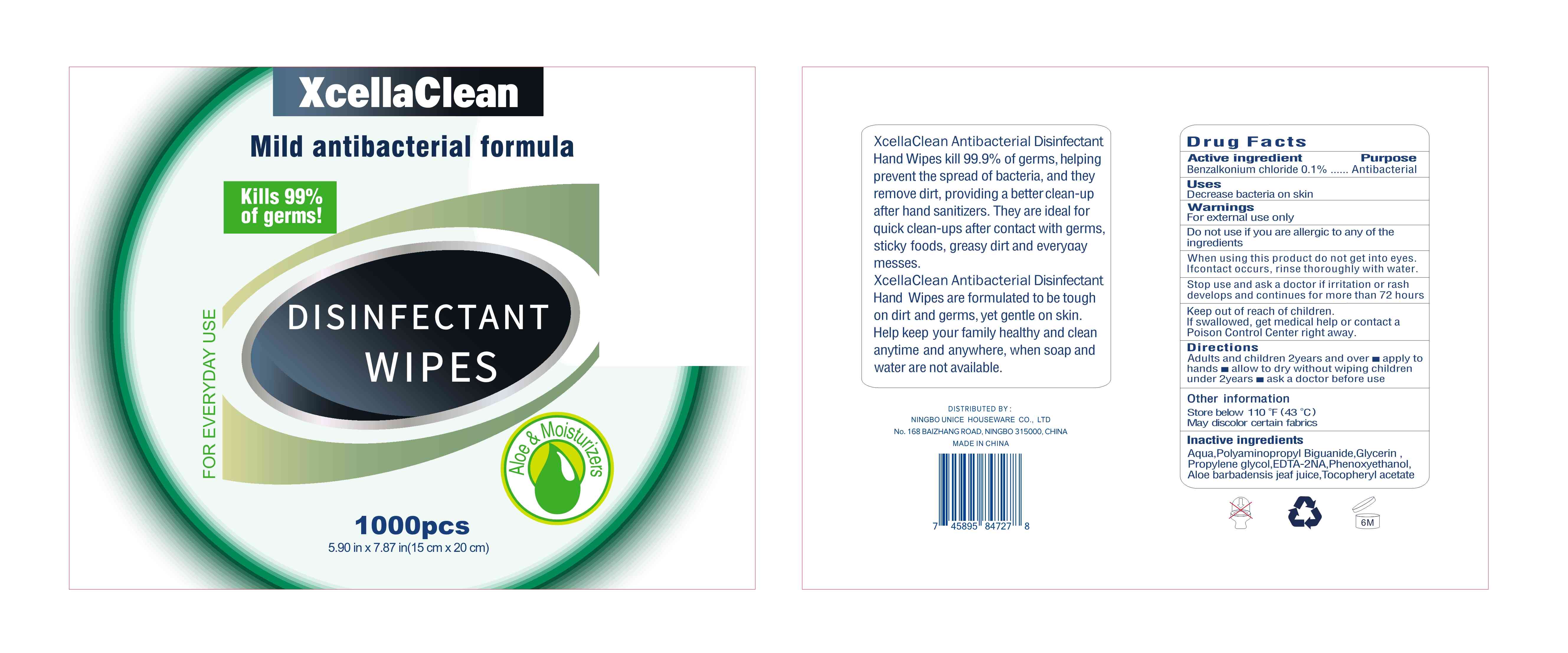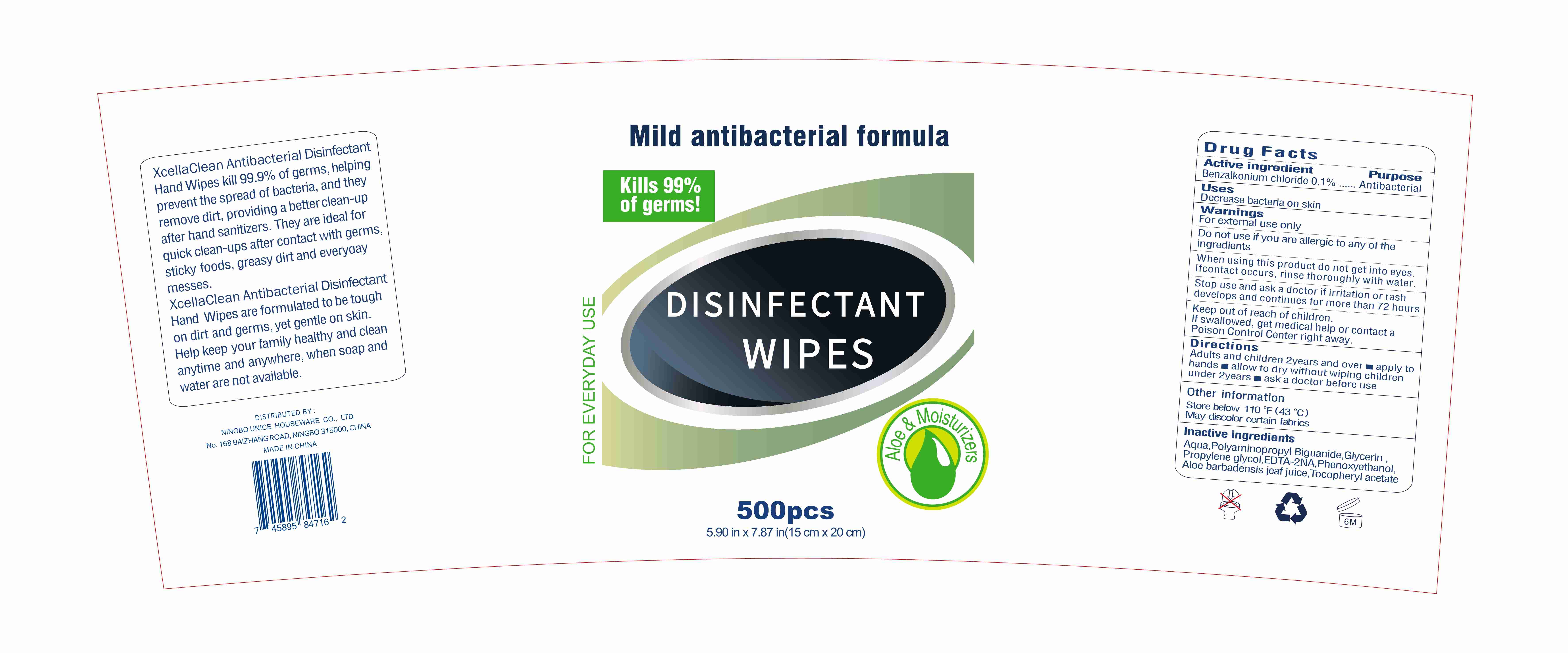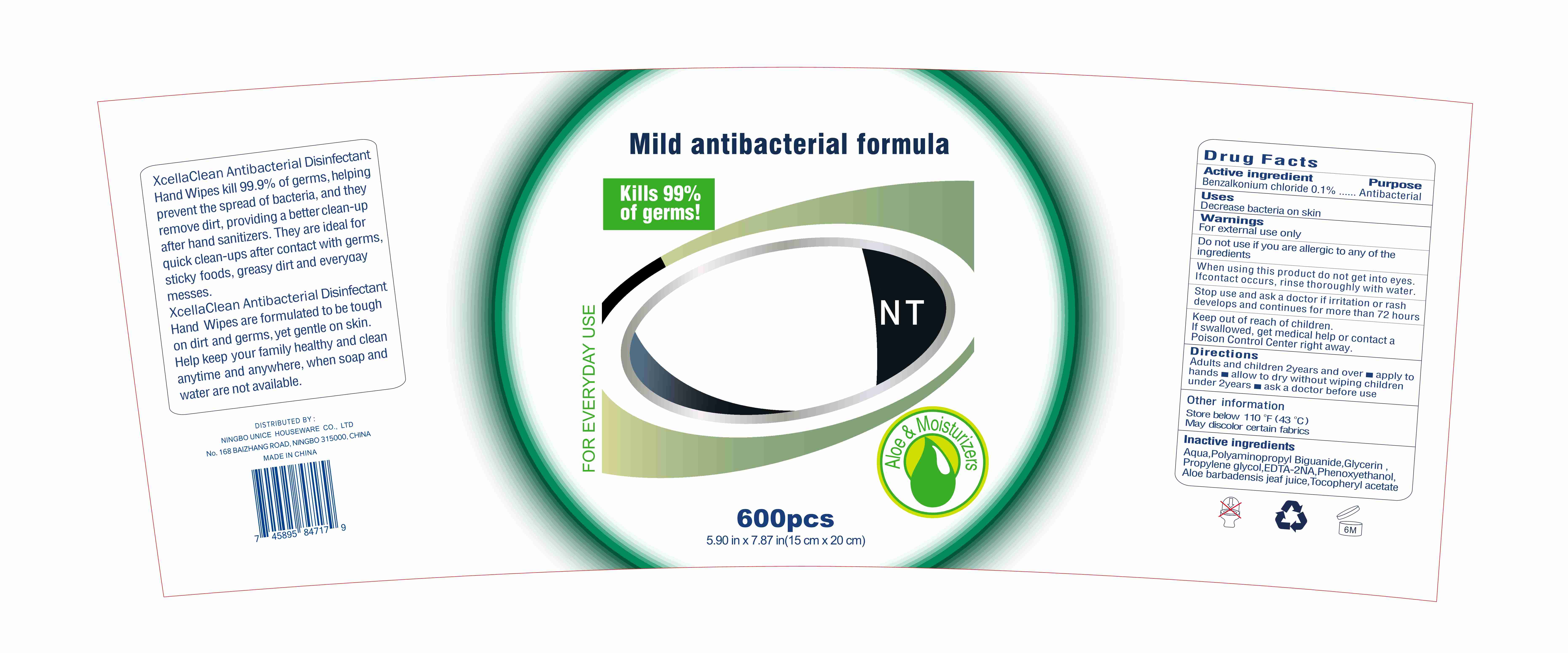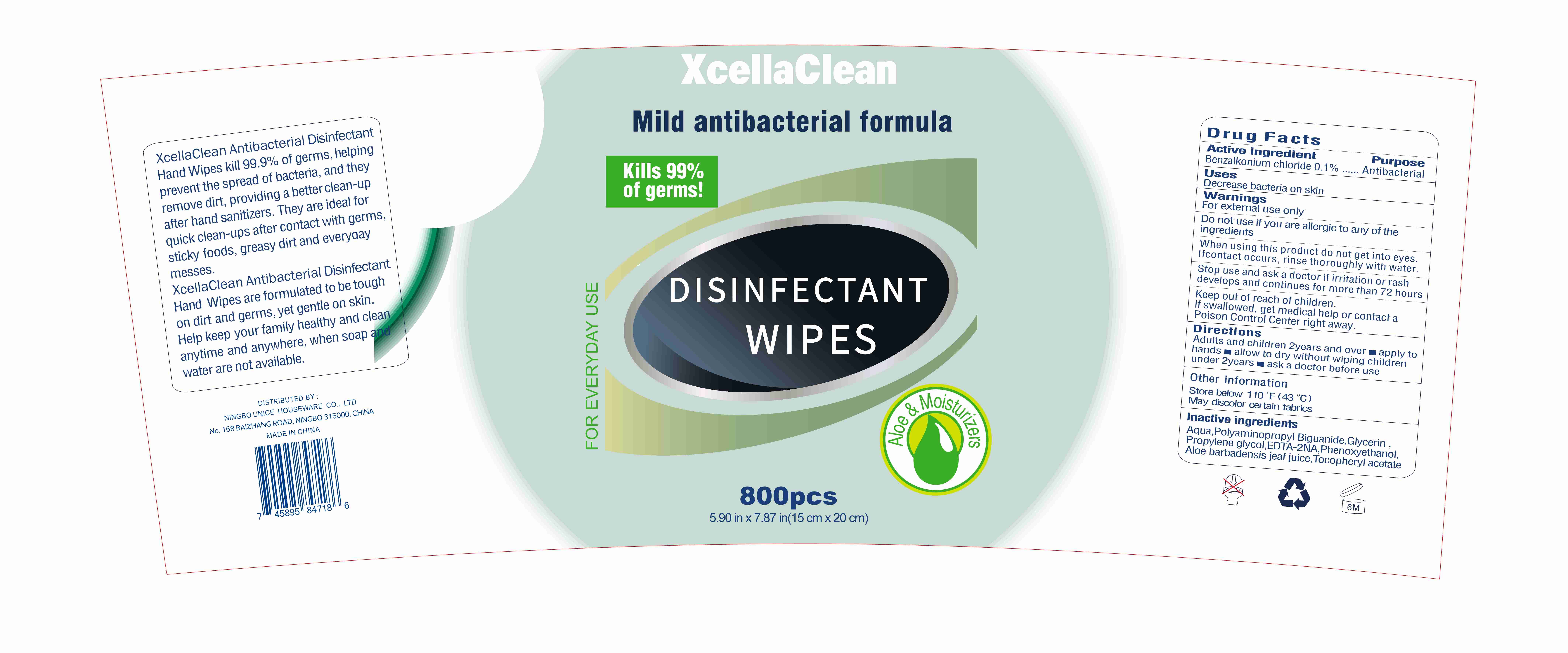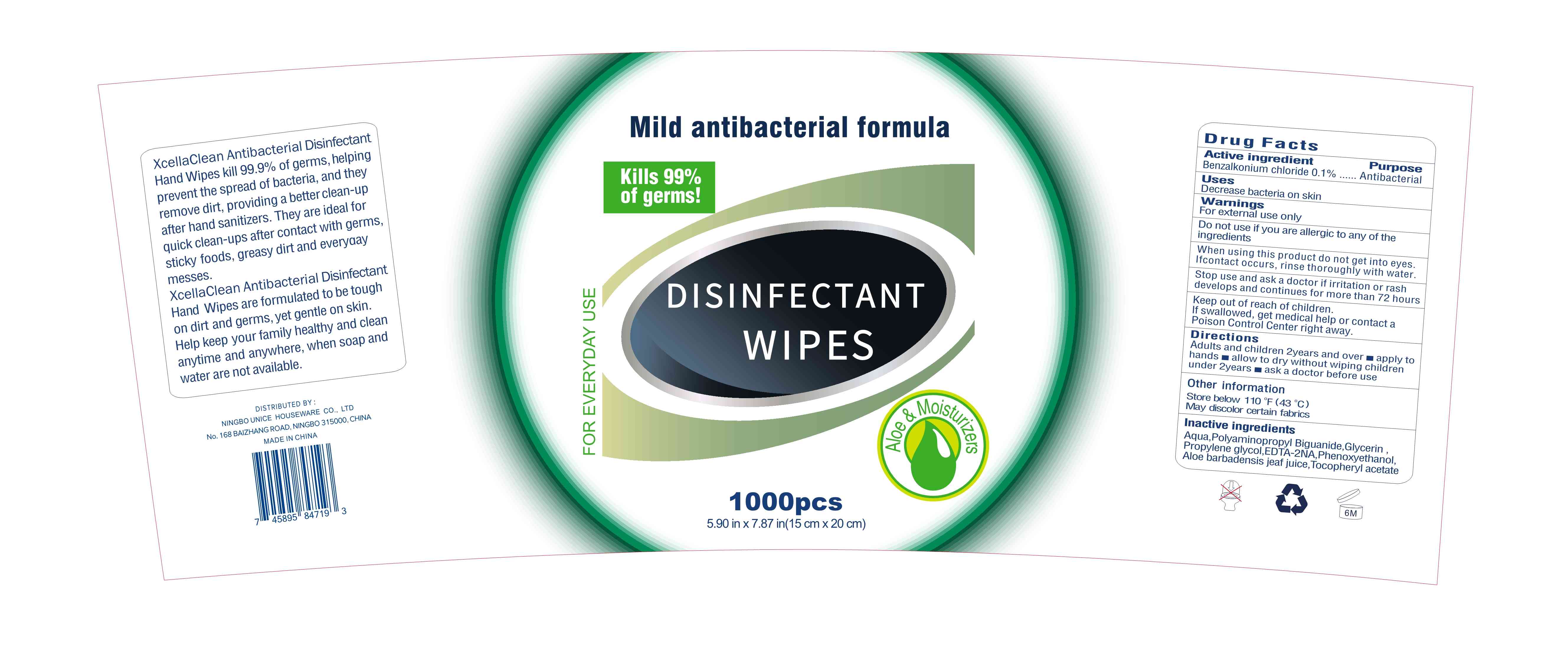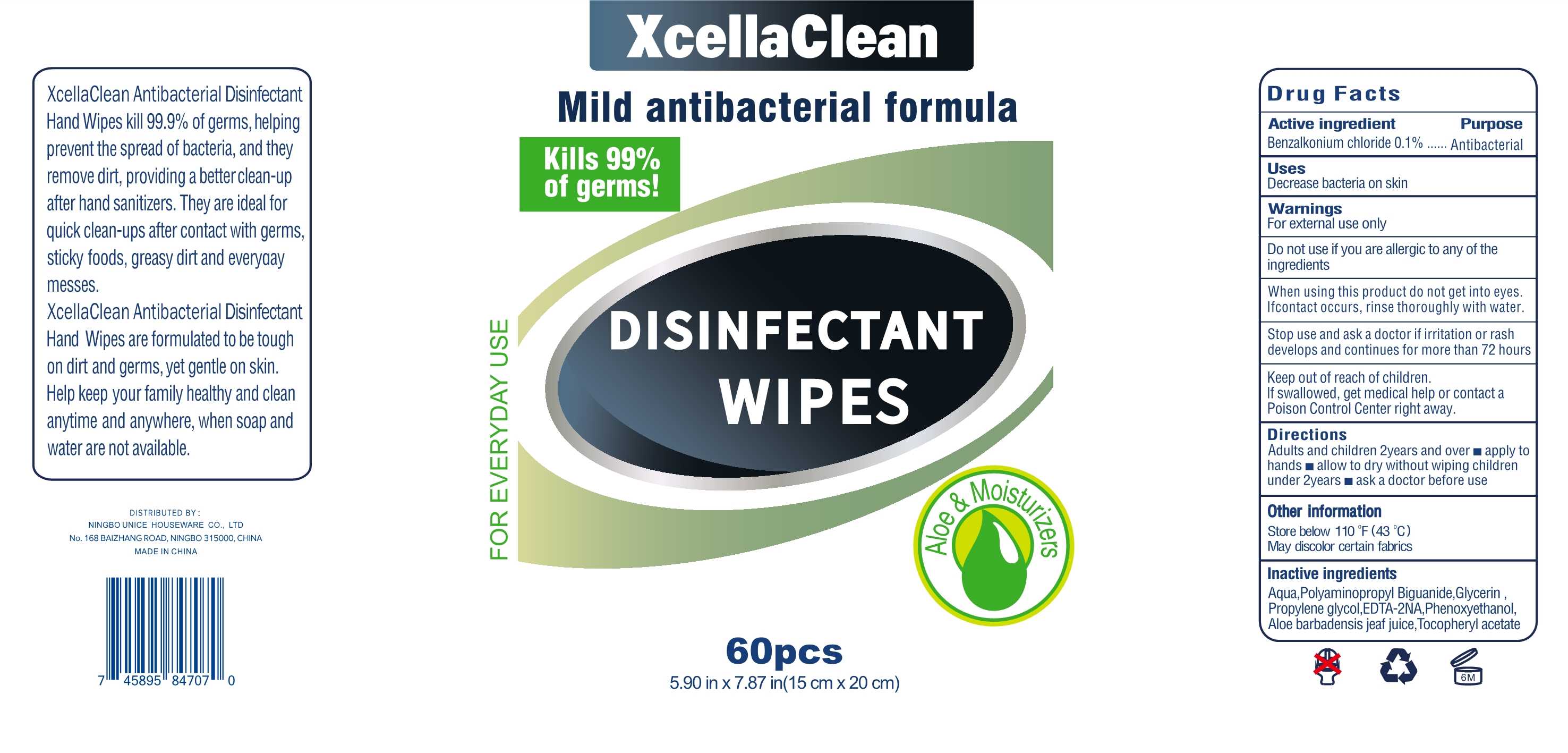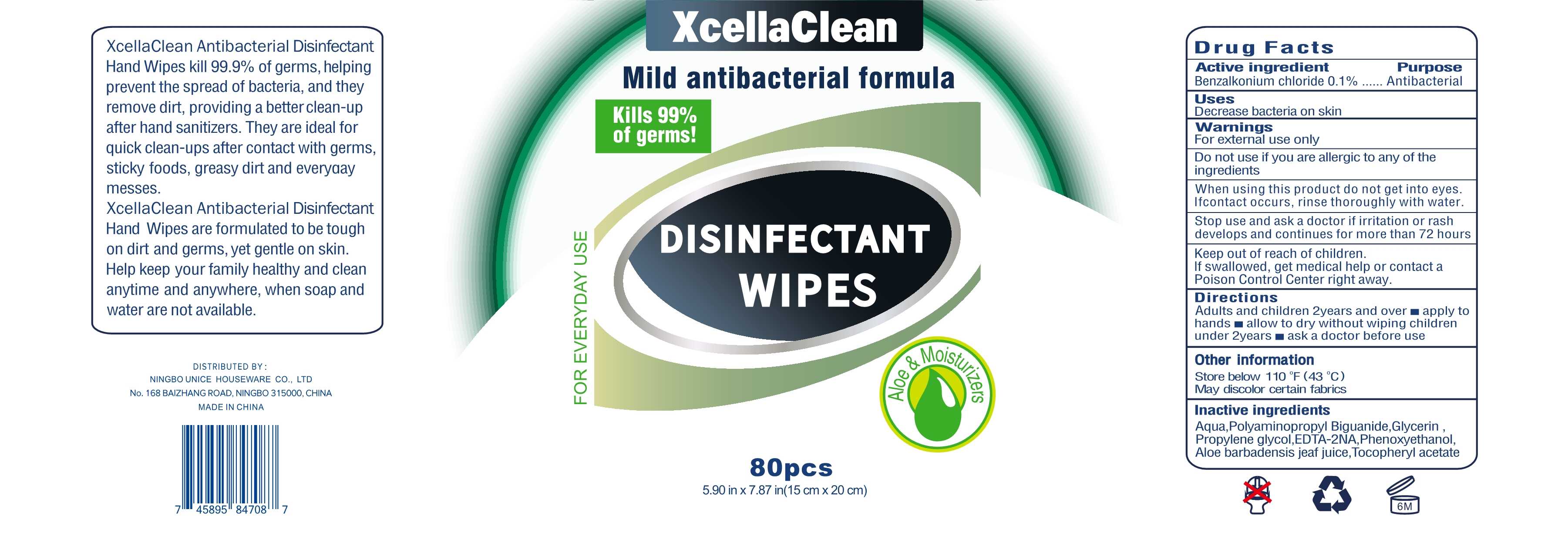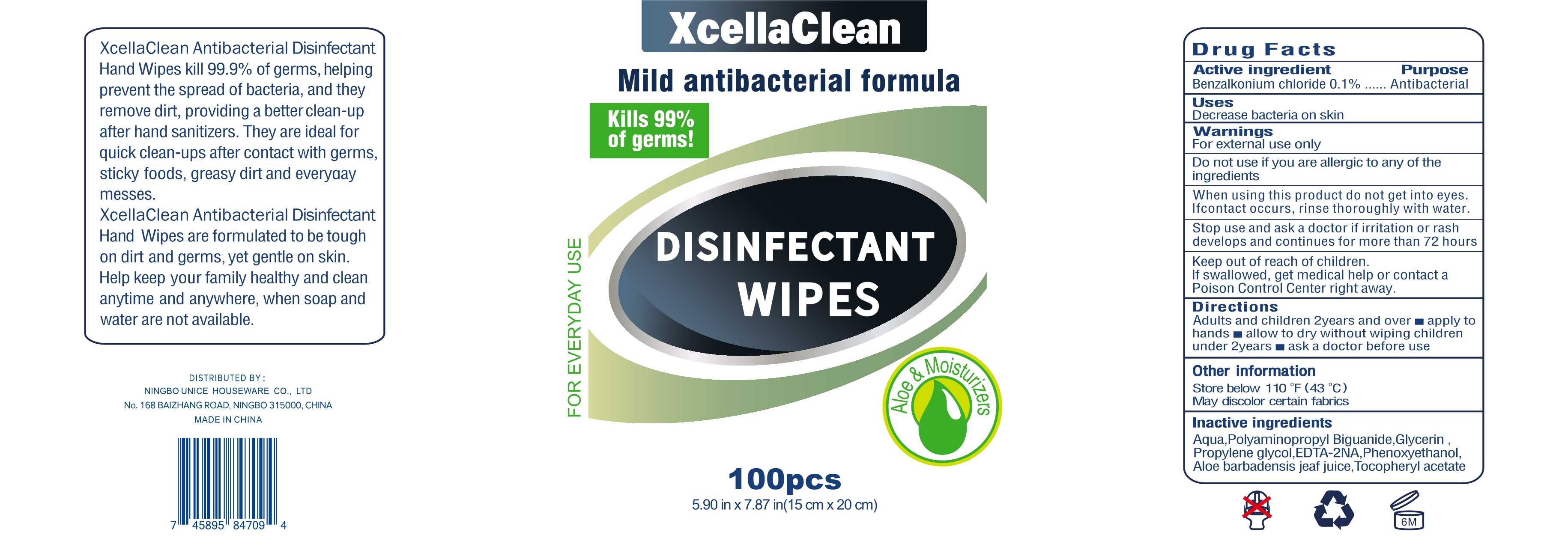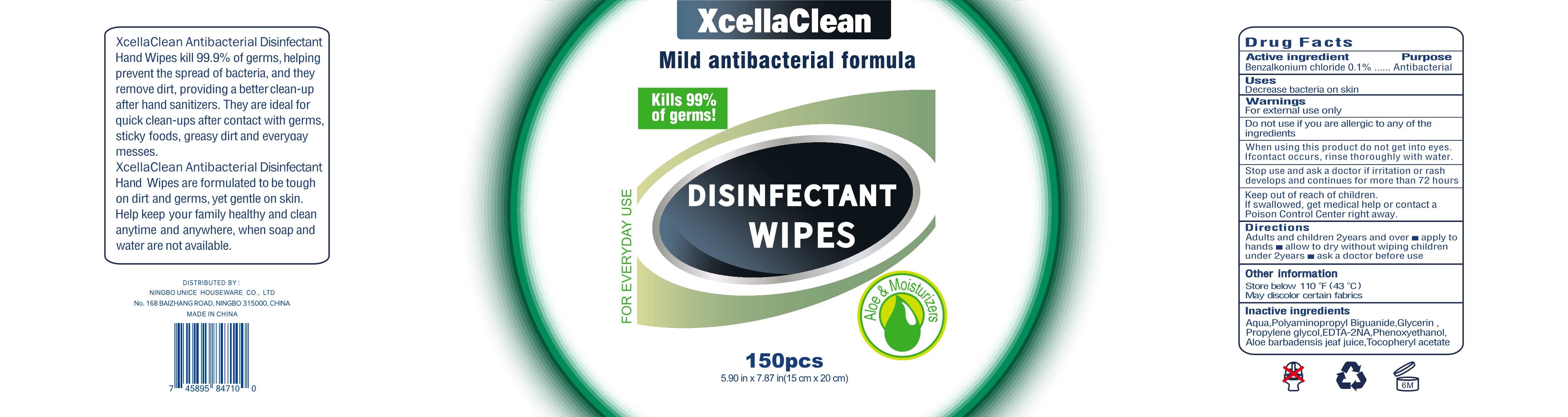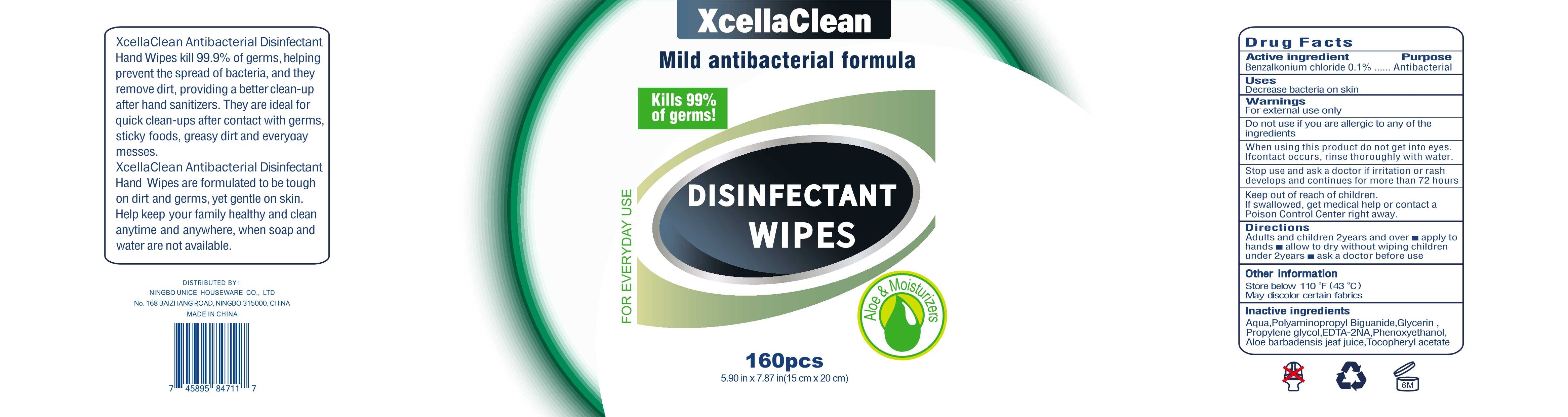 DRUG LABEL: Disinfectant Wipes
NDC: 77765-013 | Form: CLOTH
Manufacturer: Hangzhou Beitai Daily Commodity Co., Ltd.
Category: otc | Type: HUMAN OTC DRUG LABEL
Date: 20200830

ACTIVE INGREDIENTS: BENZALKONIUM CHLORIDE 0.1 g/100 1
INACTIVE INGREDIENTS: .ALPHA.-TOCOPHEROL ACETATE; POLYAMINOPROPYL BIGUANIDE; GLYCERIN; PROPYLENE GLYCOL; WATER; ALOE VERA LEAF; EDETIC ACID; PHENOXYETHANOL

77765-013
Disinfectant Wipes

Active Ingredient(s)

Benzalkonium chloride 0.1%

Purpose

Antibacterial

Use

Decrease bacteria on skin

Warnings

For external use only

Do not use if you are allergic to any of the ingredients

When using this product do not get into eyes.
Ifcontact occurs, rinse thoroughly with water.

Stop use and ask a doctor if irritation or rash develops and C1ont inues for more than 72 hours

Keep out of reach of children.
If swallowed, get medical help or contact a
Poison Control Center right away.

Do not use if you are allergic to any of the ingredients

When using this product do not get into eyes.
If contact occurs, rinse thoroughly with water.

Stop use and ask a doctor if irritation or rash develops and C1ont inues for more than 72 hours

Keep out of reach of children.
If swallowed, get medical help or contact a
Poison Control Center right away.

Stop use and ask a doctor if irritation or rash develops and C1ont inues for more than 72 hours

Keep out of reach of children.
If swallowed, get medical help or contact a
Poison Control Center right away.

Directions

Adults and children 2years and over
apply to hands
allow to dry without wiping children under 2years
ask a doctor before use

Other information

Store below 110°F (43°C)
May discolor certain fabrics

Inactive ingredients

Aqua,Polyaminopropyl Biguanide,Glycerin， Propylene gllycol,EDTA-2NA,Phenoxyethanol, Aloe barbadensis jeaf juice,Tocopheryl acetate